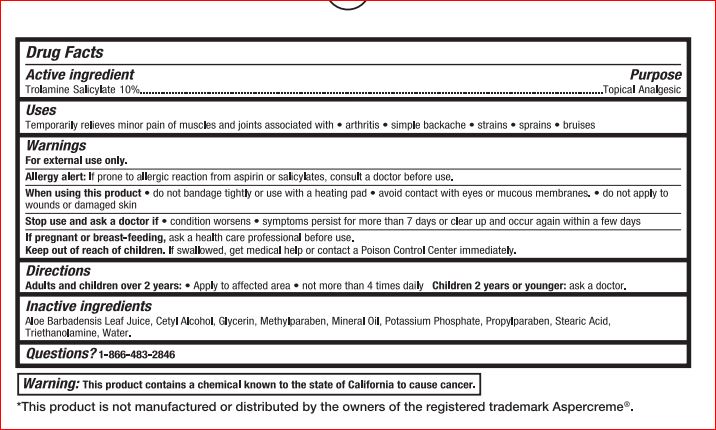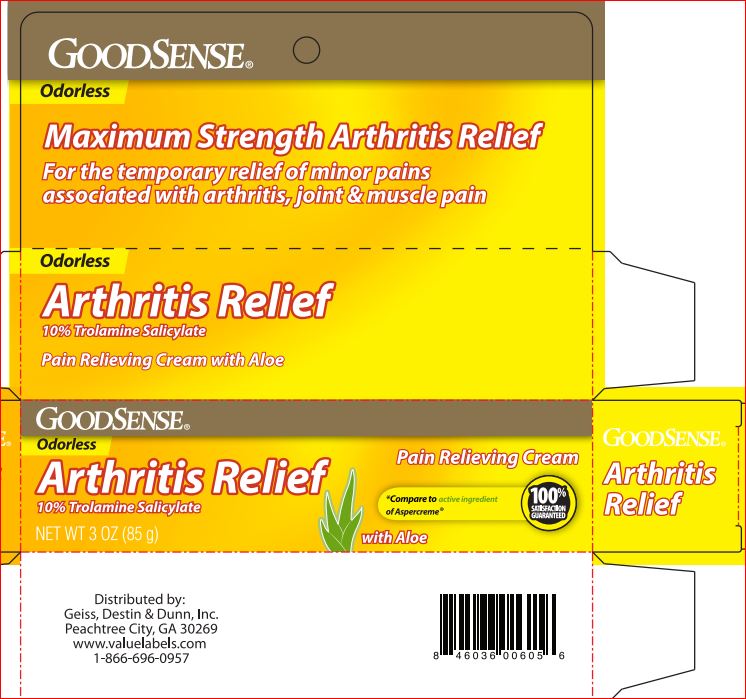 DRUG LABEL: Arthritis Relief
NDC: 50804-782 | Form: CREAM
Manufacturer: Good Sense
Category: otc | Type: HUMAN OTC DRUG LABEL
Date: 20180709

ACTIVE INGREDIENTS: TROLAMINE SALICYLATE 10 g/100 g
INACTIVE INGREDIENTS: ALOE VERA LEAF; Cetyl Alcohol; Glycerin; Methylparaben; Mineral Oil; POTASSIUM PHOSPHATE, UNSPECIFIED FORM; Propylparaben; Stearic Acid; TROLAMINE; Water

Drug Facts

Active ingredient Purpose

Trolamine Salicylate - 10% Topical Analgesic

Directions
Adults and children over 2 years: • Apply to affected area not more than 4 times daily Children 2 years or younger: ask a doctor.

INDICATIONS AND USAGE

Uses temporarily reliefs minor pain associated with • arthritis • simple backache •muscle strains • bruises • cramps

Warnings For external use only

Allergy alert: if prone to allergic reaction from aspirin or salicylates, consult a doctor before use.

When using this product • use only as directed • avoid taking a bath or shower within 1 hour before or after applying • do not bandage tightly or use with a heating pad • avoid contact with eyes or muscous membranes • do not apply to wounds or damaged skin

Stop use and ask a doctor if • condition worsens • symptoms persist for more than 7 days or clear up and occur again within a few days • redness is present • irritation develops

If pregnant or breast-feeding, ask a health professional before use.

KEEP OUT OF REACH OF CHILDREN

Keep out of reach of the children. If product is swallowed, get medical help or contact a Poison Control Center right away

Inactive ingredients

Aloe Barbadensis Leaf Juice, Cetyl Alcohol, Glycerin, Methylparaben, Mineral Oil, Potassium Phosphate, Propylparaben, Stearic Acid, Triethanolamine, Water